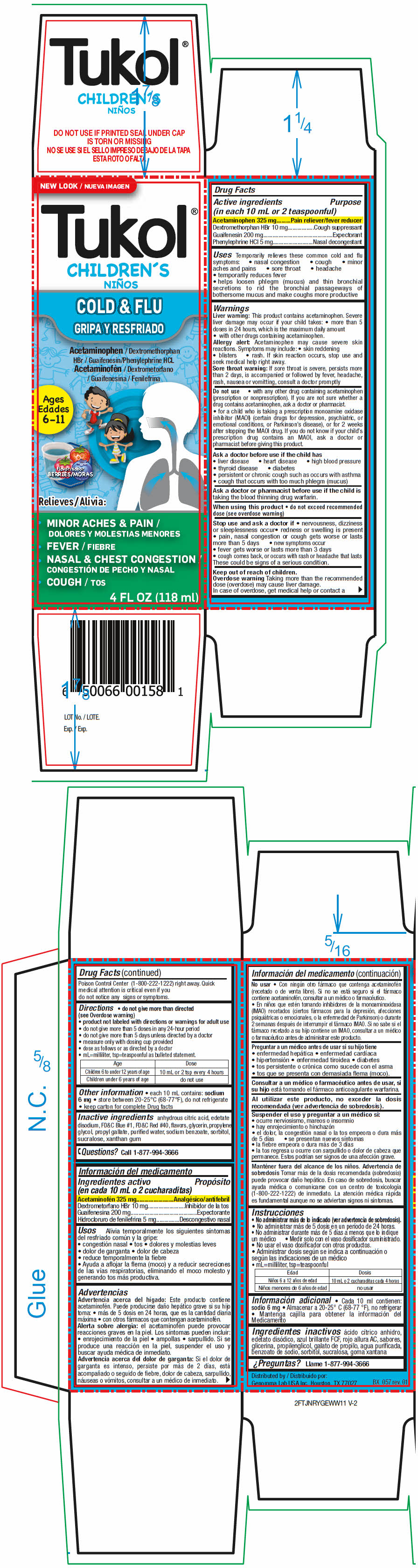 DRUG LABEL: Tukol Childrens Cold and Flu
NDC: 50066-315 | Form: SYRUP
Manufacturer: Genomma Lab USA
Category: otc | Type: HUMAN OTC DRUG LABEL
Date: 20230118

ACTIVE INGREDIENTS: Acetaminophen 32.5 mg/1 mL; Dextromethorphan Hydrobromide 1.0 mg/1 mL; Guaifenesin 20.0 mg/1 mL; PHENYLEPHRINE HYDROCHLORIDE 0.5 mg/1 mL
INACTIVE INGREDIENTS: WATER; Glycerin; Propylene Glycol; Sorbitol; Sodium benzoate; Sucralose

Tukol® Children's Cold & Flu

Drug Facts

ACTIVE INGREDIENT

PURPOSE

Active ingredients (in each 10 mL or 2 teaspoonful) | Purpose
Acetaminophen 325 mg | Pain reliever/fever reducer
Dextromethorphan HBr 10 mg | Cough suppressant
Guaifenesin 200 mg | Expectorant
Phenylephrine HCl 5 mg | Nasal decongestant

Uses

Temporarily relieves these common cold and flu symptoms:

- nasal congestion
- cough
- minor aches and pains
- sore throat
- headache
- temporarily reduces fever
- helps loosen phlegm (mucus) and thin bronchial secretions to rid the bronchial passageways of bothersome mucus and make coughs more productive

Warnings

Liver warning

This product contains acetaminophen. Severe liver damage may occur if your child takes:

- more than 5 doses in 24 hours, which is the maximum daily amount
- with other drugs containing acetaminophen.

Allergy alert

Acetaminophen may cause severe skin reactions. Symptoms may include:

- skin reddening
- blisters
- rash. If skin reaction occurs, stop use and seek medical help right away.

Sore throat warning

If sore throat is severe, persists more than 2 days, is accompanied or followed by fever, headache, rash, nausea or vomitting, consult a doctor promptly

Do not use

- with any other drug containing acetaminophen (prescription or nonprescription). If you are not sure whether a drug contains acetaminophen, ask a doctor or pharmacist.
- for a child who is taking a prescription monoamine oxidase inhibitor (MAOI) (certain drugs for depression, psychiatric, or emotional conditions, or Parkinson's disease), or for 2 weeks after stopping the MAOI drug. If you do not know if your child's prescription drug contains an MAOI, ask a doctor or pharmacist before giving this product.

Ask a doctor before use if the child has

- liver disease
- heart disease
- high blood pressure
- thyroid disease
- diabetes
- persistent or chronic cough such as occurs with asthma
- cough that occurs with too much phlegm (mucus)

Ask a doctor or pharmacist before use if the child is taking the blood thinning drug warfarin.

When using this product

- do not exceed recommended dose (see overdose warning)

Stop use and ask a doctor if

- nervousness, dizziness or sleeplessness occur
- redness or swelling is present
- pain, nasal congestion or cough gets worse or lasts more than 5 days
- new symptoms occur
- fever gets worse or lasts more than 3 days
- cough comes back, or occurs with rash or headache that lasts

These could be signs of a serious condition.

Keep out of reach of children.

Overdose warning

Taking more than the recommended dose (overdose) may cause liver damage. In case of overdose, get medical help or contact a Poison Control Center (1-800-222-1222) right away. Quick medical attention is critical even if you do not notice any signs or symptoms.

Directions

- do not give more than directed (see Overdose warning)
- product not labeled with directions or warnings for adult use
- do not give more than 5 doses in any 24-hour period
- do not give more than 5 days unless directed by a doctor
- measure only with dosing cup provided
- dose as follows or as directed by a doctor
- mL=milliliter, tsp=teaspoonful as bulleted statement.

Age | Dose
Children 6 to under 12 years of age | 10 mL or 2 tsp every 4 hours
Children under 6 years of age | do not use

Other information

- each 10 mL contains: sodium 6 mg
- store between 20-25°C (68-77°F), do not refrigerate
- keep carton for complete Drug facts

Inactive ingredients

anhydrous citric acid, edetate disodium, FD&C Blue #1, FD&C Red #40, flavors, glycerin, propylene glycol, propyl gallate, purified water, sodium benzoate, sorbitol, sucralose, xanthan gum

Questions?

Call 1-877-994-3666

Distributed by:
Genomma Lab USA Inc.,Houston, TX 77027

PRINCIPAL DISPLAY PANEL - 118 ml Bottle Carton

NEW LOOK

Tukol®
CHILDREN'S

COLD & FLU

Acetaminophen / Dextromethorphan
HBr / Guaifenesin/Phenylephrine HCL

Ages
6-11

flavor
BERRIES

Relieves:

- MINOR ACHES & PAIN
- FEVER
- NASAL & CHEST CONGESTION
- COUGH

4 FL OZ (118 ml)